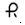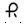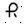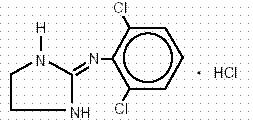 DRUG LABEL: CLONIDINE HYDROCHLORIDE
NDC: 53808-0162 | Form: TABLET
Manufacturer: State of Florida DOH Central Pharmacy
Category: prescription | Type: HUMAN PRESCRIPTION DRUG LABEL
Date: 20090620

ACTIVE INGREDIENTS: CLONIDINE HYDROCHLORIDE 0.3 mg/1 1

DESCRIPTION

Clonidine Hydrochloride is a centrally acting alpha-agonist hypotensive agent available as tablets for oral administration in three dosage strengths: 0.1 mg, 0.2 mg, and 0.3 mg. The 0.1 mg tablet is equivalent to 0.087 mg of the free base.

The following inactive ingredients are contained in these products: corn starch, D and C yellow #10 Aluminum Lake, FD and C yellow #6 Aluminum Lake (Sunset Yellow Lake), lactose monohydrate, magnesium stearate, and sodium starch glycolate.

Clonidine hydrochloride is an imidazoline derivative and exists as a mesomeric compound. The chemical name is 2-(2,6-dichlorophenylamino)-2-imidazoline hydrochloride. The following is the structural formula:

Clonidine hydrochloride is an odorless, bitter, white, crystalline substance soluble in water and alcohol.

CLINICAL PHARMACOLOGY

Clonidine stimulates alpha-adrenoreceptors in the brain stem. This action results in reduced sympathetic outflow from the central nervous system and in decreases in peripheral resistance, renal vascular resistance, heart rate, and blood pressure. Clonidine hydrochloride, acts relatively rapidly. The patient’s blood pressure declines within 30 to 60 minutes after an oral dose, the maximum decrease occurring within 2 to 4 hours. Renal blood flow and glomerular filtration rate remain essentially unchanged. Normal postural reflexes are intact, therefore, orthostatic symptoms are mild and infrequent.

Acute studies with clonidine hydrochloride in humans have demonstrated a moderate reduction (15% to 20%) of cardiac output in the supine position with no change in the peripheral resistance: at a 45° tilt there is a smaller reduction in cardiac output and a decrease of peripheral resistance. During long term therapy, cardiac output tends to return to control values, while peripheral resistance remains decreased. Slowing of the pulse rate has been observed in most patients given clonidine, but the drug does not alter normal hemodynamic response to exercise.

Tolerance to the antihypertensive effect may develop in some patients, necessitating a reevaluation of therapy.

Other studies in patients have provided evidence of a reduction in plasma renin activity and in the excretion of aldosterone and catecholamines. The exact relationship of these pharmacologic actions to the antihypertensive effect of clonidine has not been fully elucidated.

Clonidine acutely stimulates growth hormone release in both children and adults, but does not produce a chronic elevation of growth hormone with long-term use.

Pharmacokinetics: The plasma level of clonidine peaks in approximately 3 to 5 hours and the plasma half-life ranges from 12 to 16 hours. The half-life increases up to 41 hours in patients with severe impairment of renal function. Following oral administration about 40-60% of the absorbed dose is recovered in the urine as unchanged drug in 24 hours. About 50% of the absorbed dose is metabolized in the liver.

INDICATIONS AND USAGE

Clonidine hydrochloride is indicated in the treatment of hypertension. Clonidine hydrochloride may be employed alone or concomitantly with other antihypertensive agents.

CONTRAINDICATIONS

Clonidine hydrochloride tablets should not be used in patients with known hypersensitivity to clonidine (see PRECAUTIONS).

WARNINGS

Withdrawal: Patients should be instructed not to discontinue therapy without consulting their physician. Sudden cessation of clonidine treatment has, in some cases, resulted in symptoms such as nervousness, agitation, headache, and tremor accompanied or followed by a rapid rise in blood pressure and elevated catecholamine concentrations in the plasma. The likelihood of such reactions to discontinuation of clonidine therapy appears to be greater after administration of higher doses or continuation of concomitant beta-blocker treatment and special caution is therefore advised in these situations. Rare instances of hypertensive encephalopathy, cerebrovascular accidents and death have been reported after clonidine withdrawal. When discontinuing therapy with clonidine hydrochloride, the physician should reduce the dose gradually over 2 to 4 days to avoid withdrawal symptomatology.

An excessive rise in blood pressure following discontinuation of clonidine therapy can be reversed by administration of oral clonidine hydrochloride or by intravenous phentolamine. If therapy is to be discontinued in patients receiving a beta-blocker and clonidine concurrently, the beta-blocker should be withdrawn several days before the gradual discontinuation of clonidine.

Because children commonly have gastrointestinal illnesses that lead to vomiting, they may be particularly susceptible to hypertensive episodes resulting from abrupt inability to take medication.

ADVERSE REACTIONS

Most adverse effects are mild and tend to diminish with continued therapy. The most frequent (which appear to be dose-related) are dry mouth, occurring in about 40 of 100 patients; drowsiness, about 33 in 100; dizziness, about 16 in 100; constipation and sedation, each about 10 in 100.

The following less frequent adverse experiences have also been reported in patients receiving clonidine hydrochloride, but in many cases patients were receiving concomitant medication and a causal relationship has not been established.

Body As A Whole: Weakness, about 10 in 100 patients; fatigue, about 4 in 100; headache and withdrawal syndrome each about 1 in 100. Also reported were pallor; a weakly positive Coombs’ test, increased sensitivity to alcohol; and fever.

Cardiovascular: Orthostatic symptoms, about 3 in 100 patients; palpitations and tachycardia, and bradycardia, each about 5 in 1000. Syncope, Raynaud’s phenomenon, congestive heart failure, and electrocardiographic abnormalities (i.e. sinus node arrest, functional bradycardia, high degree AV block and arrhythmias) have been reported rarely. Rare cases of sinus bradycardia and atrioventricular block have been reported, both with and without the use of concomitant digitalis.

Central Nervous System: Nervousness and agitation, about 3 in 100 patients; mental depression, about 1 in 100 and insomnia, about 5 in 1000. Other behavioral changes, vivid dreams or nightmares, restlessness, anxiety, visual and auditory hallucinations and delirium have rarely been reported.

Dermatological: Rash, about 1 in 100 patients; pruritus, about 7 in 1000; hives, angioneurotic edema and urticaria, about 5 in 1000; alopecia, about 2 in 1000.

Gastrointestinal: Nausea and vomiting, about 5 in 100 patients; anorexia and malaise, each about 1 in 100; mild transient abnormalities in liver function tests, about 1 in 100; hepatitis, parotitis, constipation, pseudo-obstruction, and abdominal pain, rarely.

Genitourinary: Decreased sexual activity, impotence and loss of libido, about 3 in 100 patients; nocturia, about 1 in 100; difficulty in micturition, about 2 in 1000; urinary retention, about 1 in 1000.

Hematologic: Thrombocytopenia, rarely.

Metabolic: Weight gain, about 1 in 100 patients; gynecomastia, about 1 in 1000; transient elevation of blood glucose or serum creatine phosphokinase, rarely.

Musculoskeletal: Muscle or joint pain, about 6 in 1000 and leg cramps, about 3 in 1000.

Oro-otolaryngeal: Dryness of the nasal mucosa was rarely reported.

Ophthalmological: Dryness of eyes, burning of the eyes and blurred vision were reported.

OVERDOSAGE

Hypertension may develop early and may be followed by hypotension, bradycardia, respiratory depression, hypothermia, drowsiness, decreased or absent reflexes, weakness, irritability and miosis. The frequency of CNS depression may be higher in children than adults. Large overdoses may result in reversible cardiac conduction defects or dysrhythmias, apnea, coma and seizures. Signs and symptoms of overdose generally occur within 30 minutes to two hours after exposure. As little as 0.1 mg of clonidine has produced signs of toxicity in children.

There is no specific antidote for clonidine overdosage. Clonidine overdosage may result in the rapid development of CNS depression; therefore, induction of vomiting with ipecac syrup is not recommended. Gastric lavage may be indicated following recent and/or large ingestions. Administration of activated charcoal and/or a cathartic may be beneficial. Supportive care may include atropine sulfate for bradycardia, intravenous fluids and/or vasopressor agents for hypotension and vasodilators for hypertension. Naloxone may be a useful adjunct for the management of clonidine-induced respiratory depression, hypotension and/or coma; blood pressure should be monitored since the administration of naloxone has occasionally resulted in paradoxical hypertension. Tolazoline administration has yielded inconsistent results and is not recommended as first-line therapy. Dialysis is not likely to significantly enhance the elimination of clonidine.

The largest overdose reported to date involved a 28-year old male who ingested 100 mg of clonidine hydrochloride powder. This patient developed hypertension followed by hypotension, bradycardia, apnea, hallucinations, semicoma, and premature ventricular contractions. The patient fully recovered after intensive treatment. Plasma clonidine levels were 60 ng/ml after 1 hour, 190 ng/ml after 1.5 hours, 370 ng/ml after 2 hours, and 120 ng/ml after 5.5 and 6.5 hours. In mice and rats, the oral LD50 of clonidine is 206 and 465 mg/kg, respectively.

DOSAGE AND ADMINISTRATION

Adults: The dose of clonidine hydrochloride must be adjusted according to the patient’s individual blood pressure response. The following is a general guide to its administration.

Initial Dose: 0.1 mg tablet twice daily (morning and bedtime). Elderly patients may benefit from a lower initial dose.

Maintenance Dose: Further increments of 0.1 mg per day may be made at weekly intervals if necessary until the desired response is achieved. Taking the larger portion of the oral daily dose at bedtime may minimize transient adjustment effects of dry mouth and drowsiness. The therapeutic doses most commonly employed have ranged from 0.2 mg to 0.6 mg per day given in divided doses. Studies have indicated that 2.4 mg is the maximum effective daily dose, but doses as high as this have rarely been employed.

Renal Impairment: Dosage must be adjusted according to the degree of impairment, and patients should be carefully monitored. Since only a minimal amount of clonidine is removed during routine hemodialysis, there is no need to give supplemental clonidine following dialysis.

HOW SUPPLIED

0.1 mg — Each orange, round tablet imprinted with and 127 on one side and bisect on the other side contains 0.1 mg of Clonidine hydrochloride USP and is supplied in bottles of 100 (NDC 0228-2127-10) and 500 (NDC 0228-2127-50).

0.2 mg — Each orange, round tablet imprinted with on one side and 128 and bisect on the other side contains 0.2 mg of Clonidine hydrochloride USP and is supplied in bottles of 100 (NDC 0228-2128-10) and 500 (NDC 0228-2128-50).

0.3 mg — Each orange, round tablet imprinted with on one side and 129 and bisect on the other side contains 0.3 mg of Clonidine hydrochloride USP and is supplied in bottles of 100 (NDC 0228-2129-10).

Dispense in a tight, light-resistant container as defined in the USP.

Store at 25°C (77°F); excursions permitted to 15° to 30°C (59° to 86°F).

Manufactured by:
Actavis Elizabeth LLC
200 Elmora Avenue
Elizabeth, NJ 07207 USA
40-9009
Revised — January 2008